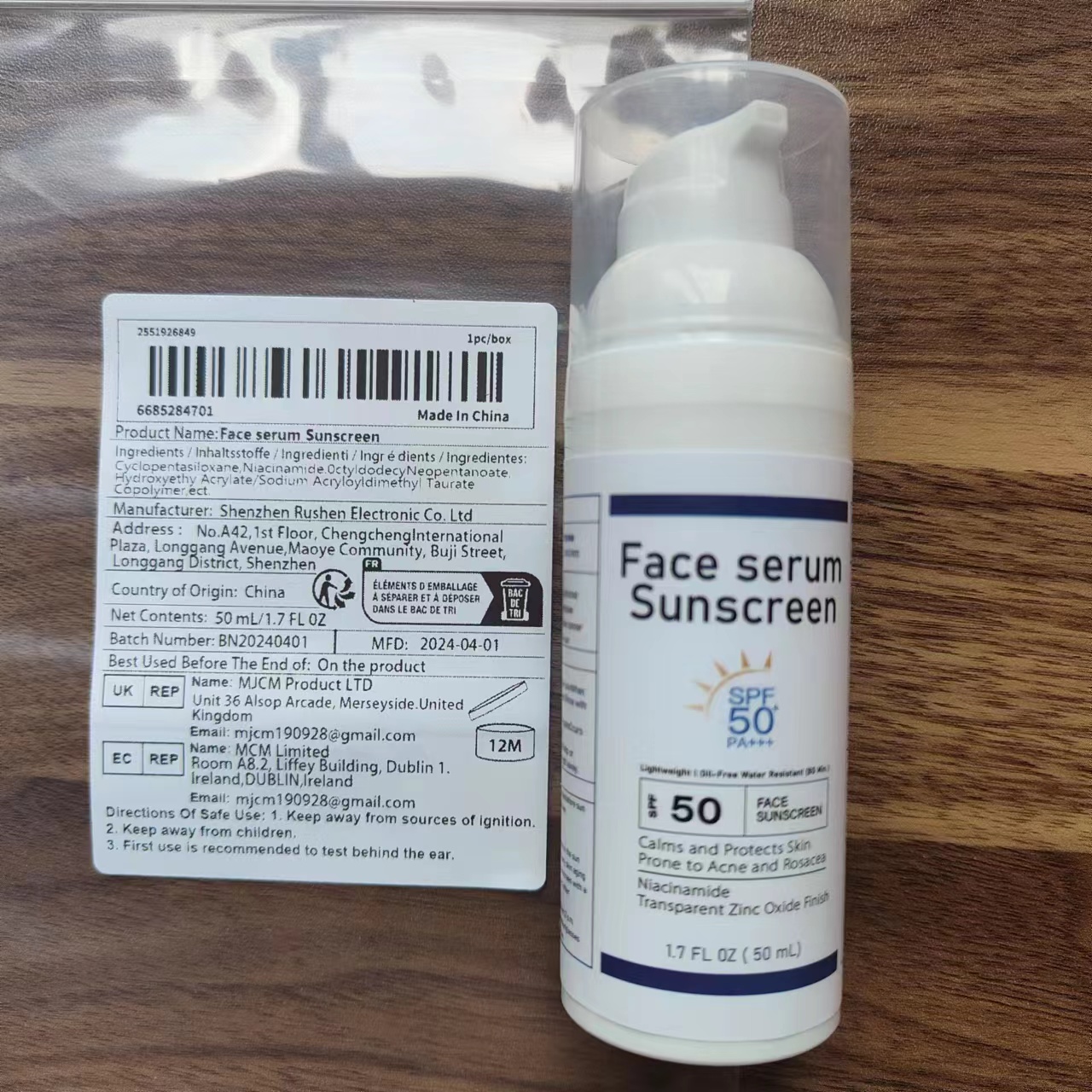 DRUG LABEL: Face Sunscreen
NDC: 84431-001 | Form: CREAM
Manufacturer: Shenzhen Rushen E-commerce Co.. Ltd.
Category: otc | Type: HUMAN OTC DRUG LABEL
Date: 20240619

ACTIVE INGREDIENTS: OCTINOXATE 7.5 mg/1 g; ZINC OXIDE 9 mg/1 g
INACTIVE INGREDIENTS: HYDROGENATED POLYISOBUTENE (1300 MW); NIACINAMIDE; BUTYLENE GLYCOL; PHENOXYETHANOL

ACTIVE INGREDIENT

Zinc Oxide 9.0%
Octinoxate 7.5%

PURPOSE

Sunscreen
Moisturizes throughout theday & helps protects

Uses

Apply sunscreen generously to exposedskin. Rub it in evenly. Reapply as neededespecially after swimming or sweating.Enjoy your sun-protected day!

Wamings

For exteral use only

Do not use
on damaged or broken skin

When using this product
Only for external use. do not ingest.
Avoid direct contact with eyes.

Stop use and ask a doctor if
rash occurs

Keep out of reach of children.
if swallowed, get medical help or contact a Poison Control Center right away.

Ask Doctor
When Pregnant or breast-feeding.

Directions
Directions for use
-apply liberally 15 minutes before sun exposure.
-reapply at least every 2 hours.
-use a water resistant sunscreen if swimming or sweating.
-Sun Protection Measures: Spending time in the sun increases your risk of skin cancer and early skin aging
-To decrease this risk, regularly use a sunscreen with a B road.
-Spectrum SPF value of15 or higher and other sun protection：
-limit time in the sun, especially from 10 a.m.-2 p.m.
-and wear long-sleeved shirts, pants, hats, and sunglasses

Other information
Before use, read all information on thecarton Store at controlled room temperature20 to 25 C (68 to 77°F)

Inactive ingredients

Water, Glycerin, Cetearyl Alcohol, Butylene Glycol,Niacinamide, Sodium Hyaluronate, Tocopherol, Centella,Asiatica Extract,Camellia Sinensis Leaf Extract,Ethylhexylglycerin, Carbomer, Triethoxycaprylyisilane,Phenoxyethanol,Xanthan Gum,Additional Ingredients(Fragrances,Stabilizers,etc.),Dibutyl Adipate,Polymethylsiisesquioxane,Coco-Caprylate/Caprate,Hyalur